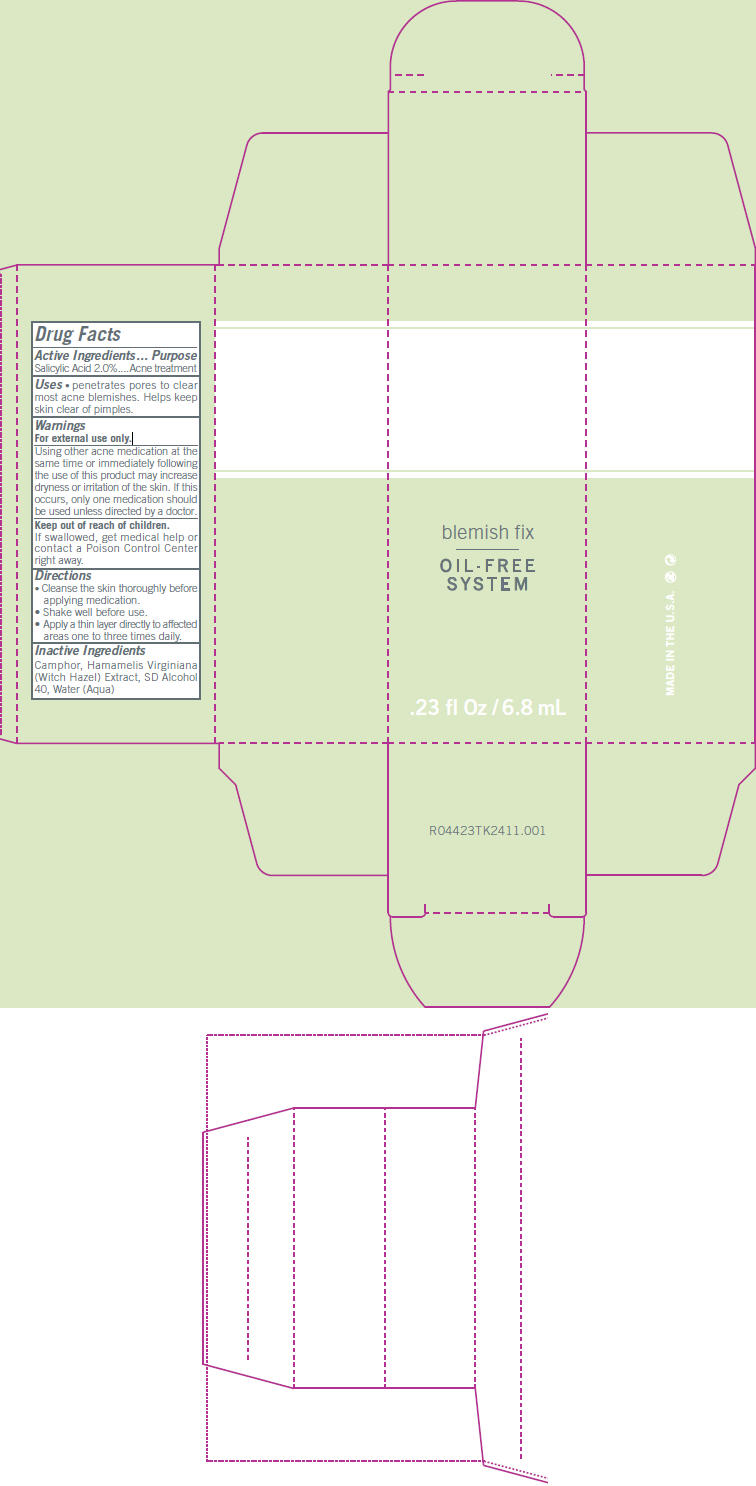 DRUG LABEL: R-044 Blemish Fix
NDC: 24623-044 | Form: LIQUID
Manufacturer: CBI Laboratories, Inc
Category: otc | Type: HUMAN OTC DRUG LABEL
Date: 20110105

ACTIVE INGREDIENTS: SALICYLIC ACID 2 mg/1 mL
INACTIVE INGREDIENTS: CAMPHOR (NATURAL); HAMAMELIS VIRGINIANA ROOT BARK/STEM BARK; WATER

blemish fix
OIL - FREE
SYSTEM

Drug Facts

Active Ingredients

Salicylic Acid 2.0%

Purpose

Acne treatment

Uses

- penetrates pores to clear most acne blemishes. Helps keep skin clear of pimples.

Warnings

For external use only.

WHEN USING

Using other acne medication at the same time or immediately following the use of this product may increase dryness or irritation of the skin. If this occurs, only one medication should be used unless directed by a doctor.

Keep out of reach of children.

If swallowed, get medical help or contact a Poison Control Center right away.

Directions

- Cleanse the skin thoroughly before applying medication.
- Shake well before use.
- Apply a thin layer directly to affected areas one to three times daily.

Inactive Ingredients

Camphor, Hamamelis Virginiana (Witch Hazel) Extract, SD Alcohol 40, Water (Aqua)

PRINCIPAL DISPLAY PANEL - 6.8 mL Carton

blemish fix

OIL - FREE
SYSTEM

.23 fl Oz / 6.8 mL